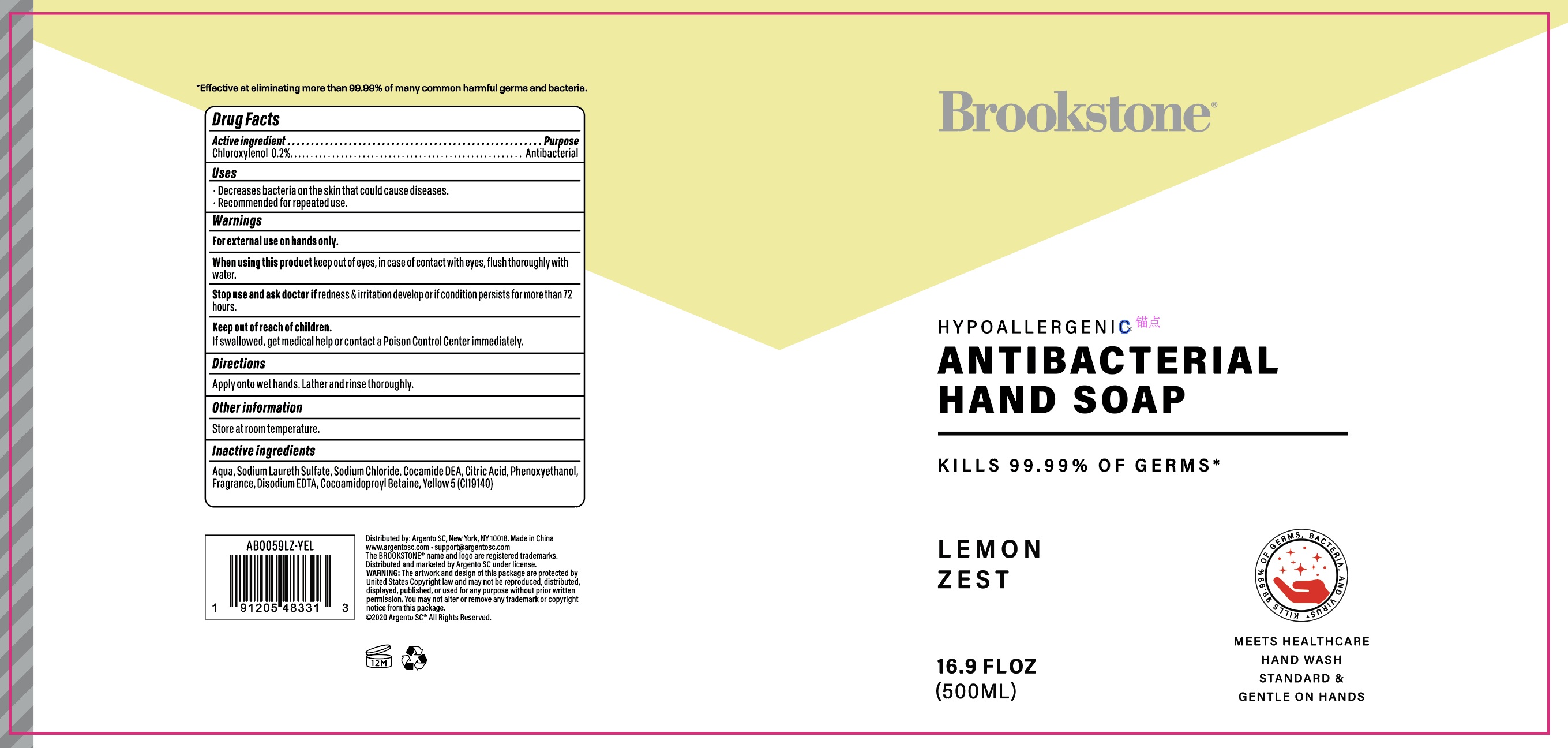 DRUG LABEL: Brookstone Lemon Zest Hypoallergenic Antibacterial Hand
NDC: 77731-093 | Form: SOAP
Manufacturer: Argento sc by sicura inc.
Category: otc | Type: HUMAN OTC DRUG LABEL
Date: 20200917

ACTIVE INGREDIENTS: CHLOROXYLENOL 0.2 g/100 mL
INACTIVE INGREDIENTS: SODIUM LAUROAMPHOACETATE; SODIUM CHLORIDE; WATER; COCAMIDOPROPYL BETAINE; PHENOXYETHANOL; CITRIC ACID MONOHYDRATE; DISODIUM HEDTA; FD&C YELLOW NO. 5

77731-093/AB0059LZ-YEL soap

Active Ingredient(s)

Chloroxylenol 0.2%

Purpose:

Antibacterial

Use

Decreases bacteria on skin that could cause diseases

Recommended for repeated use

Warnings

For external use on hands only.

When using this product, keep out of eyes. In case of contact with eyes, flush thoroughly with water

Stop use and ask a doctor

if irrigation and redness develop or if condition persists for more than 72 hours

Keep out of reach of children

If swallowed, get medical help or contact a Poison Control Center immediately

Directions

- Apply onto wet hands. Lather and rinse thoroughly

Other information

Store at room temperature

Inactive ingredients

Water, Sodium lauroamphoacetate, Sodium Chloride, Cocamide DEA, Citric acid, Phenoxyethanol, Fragrance, Disodium EDTA, Cocamidopropyl betaine, Yellow 5 (CI19140)